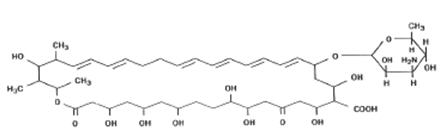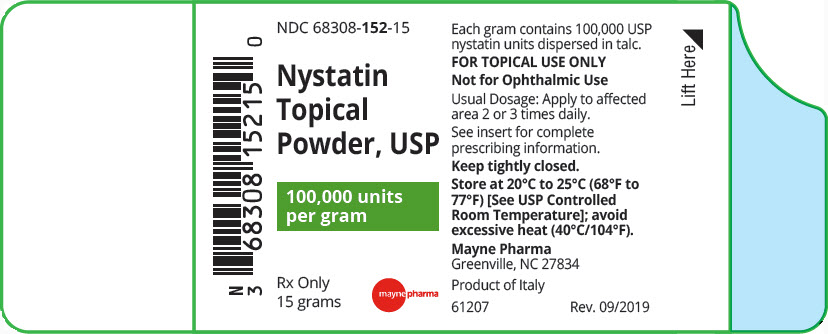 DRUG LABEL: Nystatin
NDC: 68308-152 | Form: POWDER
Manufacturer: Mayne Pharma Inc.
Category: prescription | Type: HUMAN PRESCRIPTION DRUG LABEL
Date: 20260219

ACTIVE INGREDIENTS: Nystatin 100000 [USP'U]/1 g
INACTIVE INGREDIENTS: Talc

NYSTATIN TOPICAL POWDER, USP

Rx Only

FOR TOPICAL USE ONLY.
NOT FOR OPHTHALMIC USE.

DESCRIPTION

Nystatin is a polyene antifungal antibiotic obtained from Streptomyces noursei. The molecular formula for Nystatin is C47H75NO17. The molecular weight of Nystatin is 926.1.

Structural formula:

Nystatin topical powder is for dermatologic use.

Nystatin topical powder contains 100,000 USP nystatin units per gram dispersed in talc.

CLINICAL PHARMACOLOGY

Pharmacokinetics

Nystatin is not absorbed from intact skin or mucous membrane.

Microbiology

Nystatin is an antibiotic which is both fungistatic and fungicidal in vitro against a wide variety of yeasts and yeast-like fungi, including Candida albicans, C. parapsilosis, C. tropicalis, C. guilliermondi, C. pseudotropicalis, C. krusei, Torulopsis glabrata, Tricophyton rubrum, T. mentagrophytes.

Nystatin acts by binding to sterols in the cell membrane of susceptible species resulting in a change in membrane permeability and the subsequent leakage of intracellular components. On repeated subculturing with increasing levels of nystatin, Candida albicans does not develop resistance to nystatin. Generally, resistance to nystatin does not develop during therapy. However, other species of Candida (C. tropicalis, C. guilliermondi, C. krusei, and C. stellatoides) become quite resistant on treatment with nystatin and simultaneously become cross resistant to amphotericin as well. This resistance is lost when the antibiotic is removed.

Nystatin exhibits no appreciable activity against bacteria, protozoa, or viruses.

Susceptibility Testing

For specific information regarding susceptibility test interpretive criteria, and associated test methods and quality control standards recognized by FDA for this drug, please see: http://www.fda.gov/STIC.

INDICATIONS AND USAGE

Nystatin topical powder is indicated in the treatment of cutaneous or mucocutaneous mycotic infections caused by Candida albicans and other susceptible Candida species.

Nystatin topical powder is not indicated for systemic, oral, intravaginal or ophthalmic use.

CONTRAINDICATIONS

Nystatin topical powder is contraindicated in patients with a history of hypersensitivity to any of its components.

PRECAUTIONS

General

Nystatin topical powder should not be used for the treatment of systemic, oral, intravaginal or ophthalmic infections.

If irritation or sensitization develops, treatment should be discontinued and appropriate measures taken as indicated. It is recommended that KOH smears, cultures, or other diagnostic methods be used to confirm the diagnosis of cutaneous or mucocutaneous candidiasis and to rule out infection caused by other pathogens.

INFORMATION FOR THE PATIENT

Patients using this medication should receive the following information and instructions:

1. The patient should be instructed to use this medication as directed (including the replacement of missed doses). This medication is not for any disorder other than that for which it is prescribed.
2. Even if symptomatic relief occurs within the first few days of treatment, the patient should be advised not to interrupt or discontinue therapy until the prescribed course of treatment is completed.
3. If symptoms of irritation develop, the patient should be advised to notify the physician promptly.

Laboratory Tests

If there is lack of therapeutic response, KOH smears, cultures, or other diagnostic methods should be repeated.

Carcinogenesis, Mutagenesis, Impairment of Fertility

No long-term animal studies have been performed to evaluate the carcinogenic potential of nystatin. No studies have been performed to determine the mutagenicity of nystatin or its effects on male or female fertility.

Pregnancy

Teratogenic Effects

Animal reproduction studies have not been conducted with any nystatin topical preparation. It also is not known whether these preparations can cause fetal harm when used by a pregnant woman or can affect reproductive capacity. Nystatin topical powder should be prescribed for a pregnant woman only if the potential benefit to the mother outweighs the potential risk to the fetus.

Nursing Mothers

It is not known whether nystatin is excreted in human milk. Caution should be exercised when nystatin is prescribed for a nursing woman.

Pediatric Use

Safety and effectiveness have been established in the pediatric population from birth to 16 years. (See DOSAGE AND ADMINISTRATION.)

Geriatric Use

Clinical studies with nystatin topical powder did not include sufficient numbers of subjects aged 65 years and older to determine whether they respond differently than younger subjects. Other reported clinical experience has not identified differences in responses between elderly and younger patients, but greater sensitivity of some older individuals cannot be ruled out.

ADVERSE REACTIONS

The frequency of adverse events reported in patients using nystatin topical powder is less than 0.1%. The more common events that were reported include allergic reactions, burning, itching, rash, eczema, and pain on application. (See PRECAUTIONS, General.)

DOSAGE AND ADMINISTRATION

Very moist lesions are best treated with the topical dusting powder.

Adults and Pediatric Patients (Neonates and Older)

Apply to candidal lesions two or three times daily until healing is complete. For fungal infection of the feet caused by Candida species, the powder should be dusted on the feet, as well as, in all foot wear.

HOW SUPPLIED

Nystatin topical powder, USP is supplied as 100,000 units nystatin per gram in plastic squeeze bottles:

15g (NDC 68308-152-15)
30g (NDC 68308-152-30)
60g (NDC 68308-152-60)

STORAGE

Store at 20°C to 25°C (68°F to 77°F)[see USP Controlled Room Temperature]; avoid excessive heat (40°C/104°F).

Keep tightly closed.

Mayne Pharma Greenville, NC
27834
1-844-825-8500

61207 Rev. 09/2019

PRINCIPAL DISPLAY PANEL - 15 gram Bottle Label

NDC 68308-152-15

Nystatin
Topical
Powder, USP

100,000 units
per gram

Rx Only
15 grams

mayne pharma